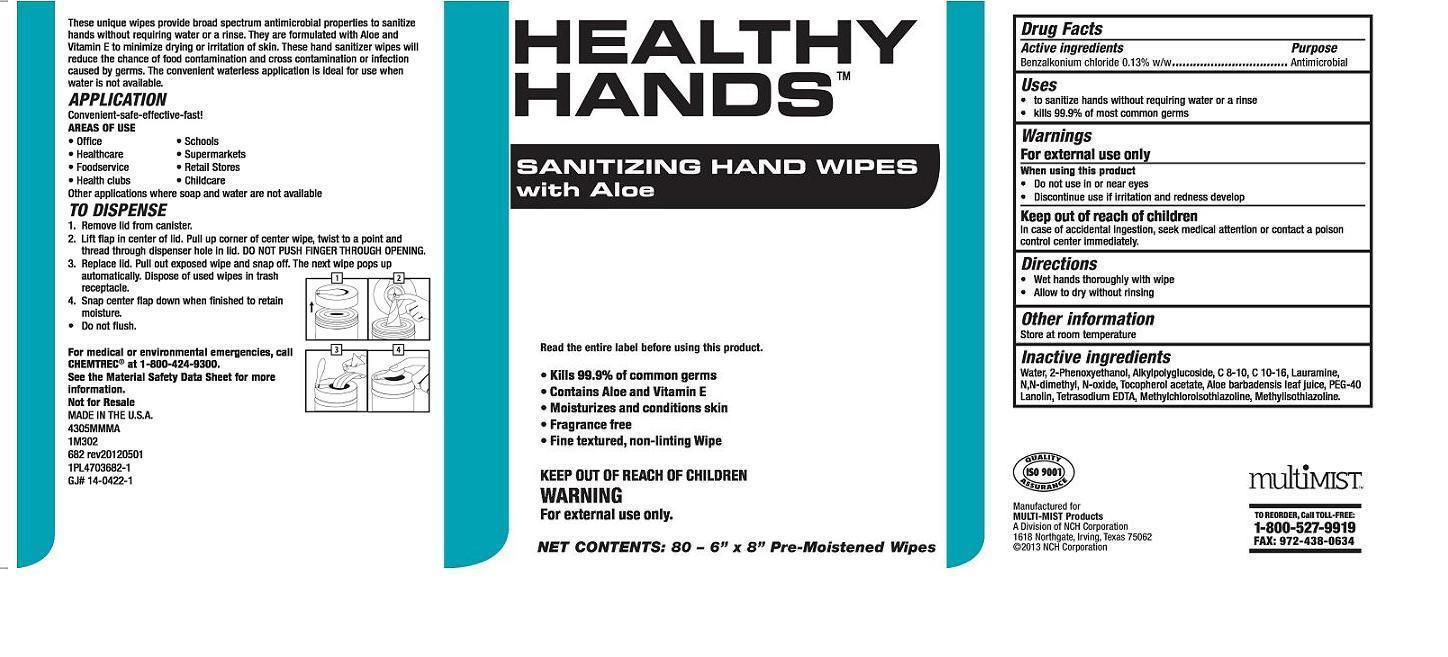 DRUG LABEL: HEALTHY HANDS SANITIZING HAND WIPES WITH ALOE
NDC: 55533-682 | Form: CLOTH
Manufacturer: NCH Corporation
Category: otc | Type: HUMAN OTC DRUG LABEL
Date: 20180207

ACTIVE INGREDIENTS: BENZALKONIUM CHLORIDE 0.0067275 g/1 1
INACTIVE INGREDIENTS: WATER; PHENOXYETHANOL; DECYL GLUCOSIDE; LAURAMINE OXIDE; ALPHA-TOCOPHEROL ACETATE; ALOE VERA LEAF; EDETATE SODIUM; METHYLCHLOROISOTHIAZOLINONE; METHYLISOTHIAZOLINONE

Drug Facts Active ingredient

Benzalkonium chloride 0.13% w/w

Purpose

Antimicrobial

Keep out of reach of children

In case of accidental ingestion, seek medical attention or contact a poison control center immediately.

Uses

 to sanitize hands without requiring water or a rinse
 kills 99.9% of most common germs

Warnings For external use only

When using this product

 do not use in or near eyes

 discontinue use if irritation and redness develop

Directions

 wet hands thoroughly with wipe  allow to dry without rinsing

Other information

 store at room temperature

Inactive ingredients:

Water, 2-Phenoxyethanol, Alkylpolyglucoside, C 8-10,C10-16, Lauramine, N,N-dimethyl, N-oxide, Tocopherol acetate, Aloe barbadensis leaf juice, PEG-40 Lanolin, Tetrasodium EDTA, Methylchloroisothiazolinone, Methylisothiazolinone.